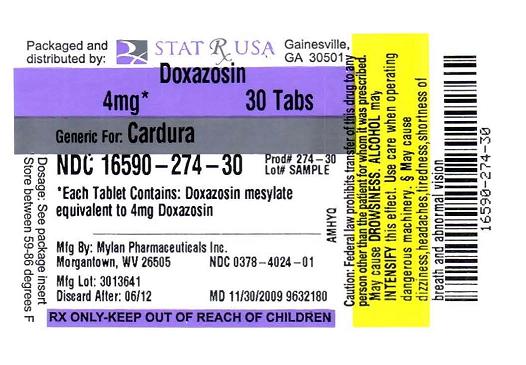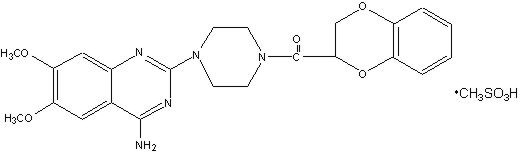 DRUG LABEL: Doxazosin
NDC: 16590-274 | Form: TABLET
Manufacturer: Stat Rx USA
Category: prescription | Type: HUMAN PRESCRIPTION DRUG LABEL
Date: 20091027

ACTIVE INGREDIENTS: Doxazosin Mesylate  4 mg/1 1

DESCRIPTION

Doxazosin mesylate is a quinazoline compound that is a selective inhibitor of the alpha1 subtype of alpha adrenergic receptors. The chemical name of doxazosin mesylate is 1-(4-amino-6,7-dimethoxy-2-quinazolinyl)-4-(1,4-benzodioxan-2-ylcarbonyl) piperazine methanesulfonate. The molecular formula for doxazosin mesylate is C23H25N5O5 • CH4O3S and the molecular weight is 547.6. It has the following structure:

Doxazosin mesylate is freely soluble in dimethylsulfoxide, soluble in dimethylformamide, slightly soluble in methanol, ethanol, and water (0.8% at 25°C), and very slightly soluble in acetone and methylene chloride.

CLINICAL PHARMACOLOGY

CLINICAL PHARMACOLOGYPharmacodynamics Benign Prostatic Hyperplasia (BPH)

Benign prostatic hyperplasia (BPH) is a common cause of urinary outflow obstruction in aging males. Severe BPH may lead to urinary retention and renal damage. A static and a dynamic component contribute to the symptoms and reduced urinary flow rate associated with BPH. The static component is related to an increase in prostate size caused, in part, by a proliferation of smooth muscle cells in the prostatic stroma. However, the severity of BPH symptoms and the degree of urethral obstruction do not correlate well with the size of the prostate. The dynamic component of BPH is associated with an increase in smooth muscle tone in the prostate and bladder neck. The degree of tone in this area is mediated by the alpha1 adrenoceptor, which is present in high density in the prostatic stroma, prostatic capsule and bladder neck. Blockade of the alpha1 receptor decreases urethral resistance and may relieve the obstruction and BPH symptoms. In the human prostate, doxazosin antagonizes phenylephrine (alpha1 agonist)-induced contractions,in vitro, and binds with high affinity to the alpha1c adrenoceptor. The receptor subtype is thought to be the predominant functional type in the prostate. Doxazosin acts within 1 to 2 weeks to decrease the severity of BPH symptoms and improve urinary flow rate. Since alpha1 adrenoceptors are of low density in the urinary bladder (apart from the bladder neck), doxazosin should maintain bladder contractility.

In BPH patients (N = 450) treated for up to 2 years in open-label studies, doxazosin therapy resulted in significant improvement above baseline in urinary flow rates and BPH symptoms. The significant effects of doxazosin were maintained over the entire treatment period.

Although blockade of alpha1 adrenoceptors also lowers blood pressure in hypertensive patients with increased peripheral vascular resistance, doxazosin treatment of normotensive men with BPH did not result in a clinically significant blood pressure lowering effect (Table 2). The proportion of normotensive patients with a sitting systolic blood pressure less than 90 mmHg and/or diastolic blood pressure less than 60 mmHg at any time during treatment with doxazosin 1 to 8 mg once daily was 6.7% with doxazosin and not significantly different (statistically) from that with placebo (5%).

Hypertension

The mechanism of action of doxazosin mesylate is selective blockade of the alpha1 (postjunctional) subtype of adrenergic receptors. Studies in normal human subjects have shown that doxazosin competitively antagonized the pressor effects of phenylephrine (an alpha1 agonist) and the systolic pressor effect of norepinephrine. Doxazosin and prazosin have similar abilities to antagonize phenylephrine. The antihypertensive effect of doxazosin results from a decrease in systemic vascular resistance. The parent compound doxazosin is primarily responsible for the antihypertensive activity. The low plasma concentrations of known active and inactive metabolites of doxazosin (2-piperazinyl, 6'- and 7'-hydroxy and 6- and 7-O-desmethyl compounds) compared to parent drug indicate that the contribution of even the most potent compound (6'-hydroxy) to the antihypertensive effect of doxazosin in man is probably small. The 6'- and 7'-hydroxy metabolites have demonstrated antioxidant properties at concentrations of 5 mcM, in vitro.

Administration of doxazosin results in a reduction in systemic vascular resistance. In patients with hypertension there is little change in cardiac output. Maximum reductions in blood pressure usually occur 2 to 6 hours after dosing and are associated with a small increase in standing heart rate. Like other alpha1-adrenergic blocking agents, doxazosin has a greater effect on blood pressure and heart rate in the standing position.

In a pooled analysis of placebo-controlled hypertension studies with about 300 hypertensive patients per treatment group, doxazosin, at doses of 1 to 16 mg given once daily, lowered blood pressure at 24 hours by about 10/8 mmHg compared to placebo in the standing position and about 9/5 mmHg in the supine position. Peak blood pressure effects (1 to 6 hours) were larger by about 50 to 75% (i.e., trough values were about 55 to 70% of peak effect), with the larger peak-trough differences seen in systolic pressures. There was no apparent difference in the blood pressure response of caucasians and blacks or of patients above and below age 65. In these predominantly normocholesterolemic patients doxazosin produced small reductions in total serum cholesterol (2 to 3%), LDL cholesterol (4%), and a similarly small increase in HDL/total cholesterol ratio (4%). The clinical significance of these findings is uncertain. In the same patient population, patients receiving doxazosin gained a mean of 0.6 kg compared to a mean loss of 0.1 kg for placebo patients.

Pharmacokinetics

After oral administration of therapeutic doses, peak plasma levels of doxazosin mesylate occur at about 2 to 3 hours. Bioavailability is approximately 65%, reflecting first pass metabolism of doxazosin by the liver. The effect of food on the pharmacokinetics of doxazosin was examined in a crossover study with 12 hypertensive subjects. Reductions of 18% in mean maximum plasma concentration and 12% in the area under the concentration-time curve occurred when doxazosin was administered with food. Neither of these differences was statistically or clinically significant.

Doxazosin is extensively metabolized in the liver, mainly by O-demethylation of the quinazoline nucleus or hydroxylation of the benzodioxan moiety. Although several active metabolites of doxazosin have been identified, the pharmacokinetics of these metabolites have not been characterized. In a study of two subjects administered radiolabelled doxazosin 2 mg orally and 1 mg intravenously on two separate occasions, approximately 63% of the dose was eliminated in the feces and 9% of the dose was found in the urine. On average only 4.8% of the dose was excreted as unchanged drug in the feces and only a trace of the total radioactivity in the urine was attributed to unchanged drug. At the plasma concentrations achieved by therapeutic doses approximately 98% of the circulating drug is bound to plasma proteins.

Plasma elimination of doxazosin is biphasic, with a terminal elimination half-life of about 22 hours. Steady-state studies in hypertensive patients given doxazosin doses of 2 to 16 mg once daily showed linear kinetics and dose proportionality. In two studies, following the administration of 2 mg orally once daily, the mean accumulation ratios (steady-state AUC vs. first dose AUC) were 1.2 and 1.7. Enterohepatic recycling is suggested by secondary peaking of plasma doxazosin concentrations.

In a crossover study in 24 normotensive subjects, the pharmacokinetics and safety of doxazosin were shown to be similar with morning and evening dosing regimens. The area under the curve after morning dosing was, however, 11% less than that after evening dosing and the time to peak concentration after evening dosing occurred significantly later than that after morning dosing (5.6 hr vs. 3.5 hr).

INDICATIONS AND USAGEBenign Prostatic Hyperplasia (BPH)

Doxazosin tablets are indicated for the treatment of both the urinary outflow obstruction and obstructive and irritative symptoms associated with BPH: obstructive symptoms (hesitation, intermittency, dribbling, weak urinary stream, incomplete emptying of the bladder) and irritative symptoms (nocturia, daytime frequency, urgency, burning). Doxazosin may be used in all BPH patients whether hypertensive or normotensive. In patients with hypertension and BPH, both conditions were effectively treated with doxazosin monotherapy. Doxazosin provides rapid improvement in symptoms and urinary flow rate in 66 to 71% of patients. Sustained improvements with doxazosin were seen in patients treated for up to 14 weeks in double-blind studies and up to 2 years in open-label studies.

Hypertension

Doxazosin tablets are also indicated for the treatment of hypertension. Doxazosin may be used alone or in combination with diuretics, beta-adrenergic blocking agents, calcium channel blockers or angiotensin-converting enzyme inhibitors.

CONTRAINDICATIONS

Doxazosin tablets are contraindicated in patients with a known sensitivity to quinazolines (e.g., prazosin, terazosin), doxazosin, or any of the inert ingredients.

WARNINGS

WARNINGSSyncope and "First-dose" Effect

Doxazosin, like other alpha-adrenergic blocking agents, can cause marked hypotension, especially in the upright position, with syncope and other postural symptoms such as dizziness. Marked orthostatic effects are most common with the first dose but can also occur when there is a dosage increase, or if therapy is interrupted for more than a few days. To decrease the likelihood of excessive hypotension and syncope, it is essential that treatment be initiated with the 1 mg dose. The 2, 4, and 8 mg tablets are not for initial therapy. Dosage should then be adjusted slowly (see DOSAGE AND ADMINISTRATION section) with evaluations and increases in dose every two weeks to the recommended dose. Additional antihypertensive agents should be added with caution.

Patients being titrated with doxazosin should be cautioned to avoid situations where injury could result should syncope occur, during both the day and night.

In an early investigational study of the safety and tolerance of increasing daily doses of doxazosin in normotensives beginning at 1 mg/day, only 2 of 6 subjects could tolerate more than 2 mg/day without experiencing symptomatic postural hypotension. In another study of 24 healthy normotensive male subjects receiving initial doses of 2 mg/day of doxazosin, seven (29%) of the subjects experienced symptomatic postural hypotension between 0.5 and 6 hours after the first dose necessitating termination of the study. In this study, 2 of the normotensive subjects experienced syncope. Subsequent trials in hypertensive patients always began doxazosin dosing at 1 mg/day resulting in a 4% incidence of postural side effects at 1 mg/day with no cases of syncope.

In multiple dose clinical trials in hypertension involving over 1,500 hypertensive patients with dose titration every one to two weeks, syncope was reported in 0.7% of patients. None of these events occurred at the starting dose of 1 mg and 1.2% (8/664) occurred at 16 mg/day.

In placebo-controlled, clinical trials in BPH, 3 out of 665 patients (0.5%) taking doxazosin reported syncope. Two of the patients were taking 1 mg doxazosin, while one patient was taking 2 mg doxazosin when syncope occurred. In the open-label, long-term extension follow-up of approximately 450 BPH patients, there were 3 reports of syncope (0.7%). One patient was taking 2 mg, one patient was taking 8 mg and one patient was taking 12 mg when syncope occurred. In a clinical pharmacology study, one subject receiving 2 mg experienced syncope.

If syncope occurs, the patient should be placed in a recumbent position and treated supportively as necessary.

Priapism

Rarely (probably less frequently than once in every several thousand patients), alpha1 antagonists, including doxazosin, have been associated with priapism (painful penile erection, sustained for hours and unrelieved by sexual intercourse or masturbation). Because this condition can lead to permanent impotence if not promptly treated, patients must be advised about the seriousness of the condition (see PRECAUTIONS: Information for Patients).

PRECAUTIONS

PRECAUTIONSGeneral Prostate Cancer

Carcinoma of the prostate causes many of the symptoms associated with BPH and the two disorders frequently co-exist. Carcinoma of the prostate should therefore be ruled out prior to commencing therapy with doxazosin.

Cataract Surgery

Intraoperative Floppy Iris Syndrome (IFIS) has been observed during cataract surgery in some patients on or previously treated with alpha1 blockers. This variant of small pupil syndrome is characterized by the combination of a flaccid iris that billows in response to intraoperative irrigation currents, progressive intraoperative miosis despite preoperative dilation with standard mydriatic drugs, and potential prolapse of the iris toward the phacoemulsification incisions. The patient's surgeon should be prepared for possible modifications to their surgical technique, such as the utilization of iris hooks, iris dilator rings, or viscoelastic substances. There does not appear to be a benefit of stopping alpha1 blocker therapy prior to cataract surgery.

Orthostatic Hypotension

While syncope is the most severe orthostatic effect of doxazosin, other symptoms of lowered blood pressure, such as dizziness, lightheadedness, or vertigo can occur, especially at initiation of therapy or at the time of dose increases.

Hypertension

These symptoms were common in clinical trials in hypertension, occurring in up to 23% of all patients treated and causing discontinuation of therapy in about 2%.

In placebo-controlled titration trials in hypertension, orthostatic effects were minimized by beginning therapy at 1 mg per day and titrating every two weeks to 2, 4, or 8 mg per day. There was an increased frequency of orthostatic effects in patients given 8 mg or more, 10%, compared to 5% at 1 to 4 mg and 3% in the placebo group.

Benign Prostatic Hyperplasia

In placebo-controlled trials in BPH, the incidence of orthostatic hypotension with doxazosin was 0.3% and did not increase with increasing dosage (to 8 mg/day). The incidence of discontinuations due to hypotensive or orthostatic symptoms was 3.3% with doxazosin and 1% with placebo. The titration interval in these studies was one to two weeks.

Patients in occupations in which orthostatic hypotension could be dangerous should be treated with particular caution. As alpha1 antagonists can cause orthostatic effects, it is important to evaluate standing blood pressure two minutes after standing and patients should be advised to exercise care when arising from a supine or sitting position.

If hypotension occurs, the patient should be placed in the supine position and, if this measure is inadequate, volume expansion with intravenous fluids or vasopressor therapy may be used. A transient hypotensive response is not a contraindication to further doses of doxazosin.

Information for Patients

(See Patient Leaflet)

Patients should be made aware of the possibility of syncopal and orthostatic symptoms, especially at the initiation of therapy, and urged to avoid driving or hazardous tasks for 24 hours after the first dose, after a dosage increase, and after interruption of therapy when treatment is resumed. They should be cautioned to avoid situations where injury could result should syncope occur during initiation of doxazosin therapy. They should also be advised of the need to sit or lie down when symptoms of lowered blood pressure occur, although these symptoms are not always orthostatic, and to be careful when rising from a sitting or lying position. If dizziness, lightheadedness, or palpitations are bothersome they should be reported to the physician, so that dose adjustment can be considered. Patients should also be told that drowsiness or somnolence can occur with doxazosin or any selective alpha1 adrenoceptor antagonist, requiring caution in people who must drive or operate heavy machinery.

Patients should be advised about the possibility of priapism as a result of treatment with alpha1 antagonists. Patients should know that this adverse event is very rare. If they experience priapism, it should be brought to immediate medical attention for if not treated promptly it can lead to permanent erectile dysfunction (impotence).

Drug/Laboratory Test Interactions

Doxazosin does not affect the plasma concentration of prostate specific antigen in patients treated for up to 3 years. Both doxazosin, an alpha1 inhibitor, and finasteride, a 5-alpha reductase inhibitor, are highly protein bound and hepatically metabolized. There is no definitive controlled clinical experience on the concomitant use of alpha1 inhibitors and 5-alpha reductase inhibitors at this time.

Impaired Liver Function

Doxazosin should be administered with caution to patients with evidence of impaired hepatic function or to patients receiving drugs known to influence hepatic metabolism (see CLINICAL PHARMACOLOGY).

Leukopenia/Neutropenia

Analysis of hematologic data from hypertensive patients receiving doxazosin in controlled hypertension clinical trials showed that the mean WBC (N = 474) and mean neutrophil counts (N = 419) were decreased by 2.4% and 1%, respectively, compared to placebo, a phenomenon seen with other alpha blocking drugs. In BPH patients the incidence of clinically significant WBC abnormalities was 0.4% (2/459) with doxazosin and 0% (0/147) with placebo, with no statistically significant difference between the two treatment groups. A search through a data base of 2,400 hypertensive patients and 665 BPH patients revealed 4 hypertensives in which drug-related neutropenia could not be ruled out and one BPH patient in which drug-related leukopenia could not be ruled out. Two hypertensives had a single low value on the last day of treatment. Two hypertensives had stable, non-progressive neutrophil counts in the 1000/mm^3 range over periods of 20 and 40 weeks. One BPH patient had a decrease from WBC count of 4800/mm^3 to 2700/mm^3 at the end of the study; there was no evidence of clinical impairment. In cases where follow-up was available the WBCs and neutrophil counts returned to normal after discontinuation of doxazosin. No patients became symptomatic as a result of the low WBC or neutrophil counts.

Drug Interactions

Most (98%) of plasma doxazosin is protein bound. In vitro data in human plasma indicate that doxazosin has no effect on protein binding of digoxin, warfarin, phenytoin or indomethacin. There is no information on the effect of other highly plasma protein bound drugs on doxazosin binding. Doxazosin has been administered without any evidence of an adverse drug interaction to patients receiving thiazide diuretics, beta-blocking agents, and nonsteroidal anti-inflammatory drugs. In a placebo-controlled trial in normal volunteers, the administration of a single 1 mg dose of doxazosin on day 1 of a 4-day regimen of oral cimetidine (400 mg twice daily) resulted in a 10% increase in mean AUC of doxazosin (p = 0.006), and a slight but not statistically significant increase in mean Cmax and mean half-life of doxazosin. The clinical significance of this increase in doxazosin AUC is unknown.

In clinical trials, doxazosin tablets have been administered to patients on a variety of concomitant medications; while no formal interaction studies have been conducted, no interactions were observed. Doxazosin tablets have been used with the following drugs or drug classes: 1) analgesic/anti-inflammatory (e.g., acetaminophen, aspirin, codeine and codeine combinations, ibuprofen, indomethacin); 2) antibiotics (e.g., erythromycin, trimethoprim and sulfamethoxazole, amoxicillin); 3) antihistamines (e.g., chlorpheniramine); 4) cardiovascular agents (e.g., atenolol, hydrochlorothiazide, propranolol); 5) corticosteroids; 6) gastrointestinal agents (e.g., antacids); 7) hypoglycemics and endocrine drugs; 8) sedatives and tranquilizers (e.g., diazepam); 9) cold and flu remedies.

Cardiac Toxicity in Animals

An increased incidence of myocardial necrosis or fibrosis was displayed by Sprague-Dawley rats after 6 months of dietary administration at concentrations calculated to provide 80 mg doxazosin/kg/day and after 12 months of dietary administration at concentrations calculated to provide 40 mg doxazosin/kg/day (AUC exposure in rats 8 times the human AUC exposure with a 12 mg/day therapeutic dose). Myocardial fibrosis was observed in both rats and mice treated in the same manner with 40 mg doxazosin/kg/day for 18 months (exposure 8 times human AUC exposure in rats and somewhat equivalent to human Cmax exposure in mice). No cardiotoxicity was observed at lower doses (up to 10 or 20 mg/kg/day, depending on the study) in either species. These lesions were not observed after 12 months of oral dosing in dogs at maximum doses of 20 mg/kg/day [maximum plasma concentrations (Cmax) in dogs 14 times the Cmax exposure in humans receiving a 12 mg/day therapeutic dose] and in Wistar rats at doses of 100 mg/kg/day (Cmax exposures 15 times human Cmax exposure with a 12 mg/day therapeutic dose). There is no evidence that similar lesions occur in humans.

Carcinogenesis, Mutagenesis, Impairment of Fertility

Chronic dietary administration (up to 24 months) of doxazosin mesylate at maximally tolerated doses of 40 mg/kg/day in rats and 120 mg/kg/day in mice revealed no evidence of carcinogenic potential. The highest doses evaluated in the rat and mouse studies are associated with AUCs (a measure of systemic exposure) that are 8 times and 4 times, respectively, the human AUC at a dose of 16 mg/day.

Mutagenicity studies revealed no drug- or metabolite-related effects at either chromosomal or subchromosomal levels.

Studies in rats showed reduced fertility in males treated with doxazosin at oral doses of 20 (but not 5 or 10) mg/kg/day, about 4 times the AUC exposures obtained with a 12 mg/day human dose. This effect was reversible within two weeks of drug withdrawal. There have been no reports of any effects of doxazosin on male fertility in humans.

Pregnancy Teratogenic Effects Pregnancy Category C

Studies in pregnant rabbits and rats at daily oral doses of up to 41 and 20 mg/kg, respectively (plasma drug concentrations 10 and 4 times human Cmax and AUC exposures with a 12 mg/day therapeutic dose), have revealed no evidence of harm to the fetus. A dosage regimen of 82 mg/kg/day in the rabbit was associated with reduced fetal survival. There are no adequate and well-controlled studies in pregnant women. Because animal reproduction studies are not always predictive of human response, doxazosin should be used during pregnancy only if clearly needed.

Radioactivity was found to cross the placenta following oral administration of labeled doxazosin to pregnant rats.

Nonteratogenic Effects

In peri-postnatal studies in rats, postnatal development at maternal doses of 40 or 50 mg/kg/day of doxazosin (8 times human AUC exposure with a 12 mg/day therapeutic dose) was delayed as evidenced by slower body weight gain and a slightly later appearance of anatomical features and reflexes.

Nursing Mothers

Studies in lactating rats given a single oral dose of 1 mg/kg of [2-^14C]-doxazosin indicate that doxazosin accumulates in rat breast milk with a maximum concentration about 20 times greater than the maternal plasma concentration. It is not known whether this drug is excreted in human milk. Because many drugs are excreted in human milk, caution should be exercised when doxazosin is administered to a nursing mother.

Pediatric Use

The safety and effectiveness of doxazosin as an antihypertensive agent have not been established in pediatric patients.

Geriatric Use

The safety and effectiveness profile of doxazosin in BPH was similar in the elderly (age ≥ 65 years) and younger (age less 65 years) patients.

Clinical studies of doxazosin did not include sufficient numbers of subjects aged 65 and over to determine whether they respond differently from younger subjects. Other reported clinical experience has not identified differences in responses between the elderly and younger patients. In general, dose selection for an elderly patient should be cautious, usually starting at the low end of the dosing range, reflecting the greater frequency of decreased hepatic, renal, or cardiac function, and of concomitant disease or other drug therapy.

ADVERSE REACTIONSBenign Prostatic Hyperplasia

The incidence of adverse events has been ascertained from worldwide clinical trials in 965 BPH patients. The incidence rates presented below (Table 3) are based on combined data from seven placebo-controlled trials involving once daily administration of doxazosin in doses of 1 to 16 mg in hypertensives and 0.5 to 8 mg in normotensives. The adverse events when the incidence in the doxazosin group was at least 1% are summarized in Table 3. No significant difference in the incidence of adverse events compared to placebo was seen except for dizziness, fatigue, hypotension, edema and dyspnea. Dizziness and dyspnea appeared to be dose-related.

In these placebo-controlled studies of 665 doxazosin patients, treated for a mean of 85 days, additional adverse reactions have been reported. These are less than 1% and not distinguishable from those that occurred in the placebo group. Adverse reactions with an incidence of less than 1% but of clinical interest are (doxazosin vs. placebo): Cardiovascular System: angina pectoris (0.6% vs. 0.7%), postural hypotension (0.3% vs. 0.3%), syncope (0.5% vs. 0.0%), tachycardia (0.9% vs. 0.0%); Urogenital System: dysuria (0.5% vs. 1.3%), and Psychiatric Disorders: libido decreased (0.8% vs. 0.3%). The safety profile in patients treated for up to three years was similar to that in the placebo-controlled studies.

The majority of adverse experiences with doxazosin were mild.

Hypertension

Doxazosin mesylate has been administered to approximately 4,000 hypertensive patients, of whom 1,679 were included in the hypertension clinical development program. In that program, minor adverse effects were frequent, but led to discontinuation of treatment in only 7% of patients. In placebo-controlled studies adverse effects occurred in 49% and 40% of patients in the doxazosin and placebo groups, respectively, and led to discontinuation in 2% of patients in each group. The major reasons for discontinuation were postural effects (2%), edema, malaise/fatigue, and some heart rate disturbance, each about 0.7%.

In controlled hypertension clinical trials directly comparing doxazosin to placebo there was no significant difference in the incidence of side effects, except for dizziness (including postural), weight gain, somnolence and fatigue/malaise. Postural effects and edema appeared to be dose related. The prevalence rates presented below are based on combined data from placebo-controlled studies involving once daily administration of doxazosin at doses ranging from 1 to 16 mg. Table 4 summarizes those adverse experiences (possibly/probably related) reported for patients in these hypertension studies where the prevalence rate in the doxazosin group was at least 0.5% or where the reaction is of particular interest.

OVERDOSAGE

Experience with doxazosin overdosage is limited. Two adolescents who each intentionally ingested 40 mg doxazosin with diclofenac or acetaminophen, were treated with gastric lavage with activated charcoal and made full recoveries. A two-year-old child who accidentally ingested 4 mg doxazosin was treated with gastric lavage and remained normotensive during the five-hour emergency room observation period. A six-month-old child accidentally received a crushed 1 mg tablet of doxazosin and was reported to have been drowsy. A 32-year-old female with chronic renal failure, epilepsy and depression intentionally ingested 60 mg doxazosin (blood level 0.9 mcg/mL; normal values in hypertensives = 0.02 mcg/mL); death was attributed to a grand mal seizure resulting from hypotension. A 39-year-old female who ingested 70 mg doxazosin, alcohol and flurazepam developed hypotension which responded to fluid therapy.

The oral LD50 of doxazosin is greater than 1000 mg/kg in mice and rats. The most likely manifestation of overdosage would be hypotension, for which the usual treatment would be intravenous infusion of fluid. As doxazosin is highly protein bound, dialysis would not be indicated.

DOSAGE AND ADMINISTRATION

DOSAGE MUST BE INDIVIDUALIZED. The initial dosage of doxazosin tablets in patients with hypertension and/or BPH is 1 mg given once daily in the a.m. or p.m. This starting dose is intended to minimize the frequency of postural hypotension and first dose syncope associated with doxazosin. Postural effects are most likely to occur between 2 and 6 hours after a dose. Therefore blood pressure measurements should be taken during this time period after the first dose and with each increase in dose. If doxazosin tablets administration is discontinued for several days, therapy should be restarted using the initial dosing regimen.

Benign Prostatic Hyperplasia 1 to 8 mg Once Daily

The initial dosage of doxazosin is 1 mg, given once daily in the a.m. or p.m. Depending on the individual patient's urodynamics and BPH symptomatology, dosage may then be increased to 2 mg and thereafter to 4 mg and 8 mg once daily, the maximum recommended dose for BPH. The recommended titration interval is 1 to 2 weeks. Blood pressure should be evaluated routinely in these patients.

Hypertension 1 to 16 mg Once Daily

The initial dosage of doxazosin is 1 mg given once daily. Depending on the individual patient's standing blood pressure response (based on measurements taken at 2 to 6 hours post-dose and 24 hours post-dose), dosage may then be increased to 2 mg and thereafter if necessary to 4 mg, 8 mg and 16 mg to achieve the desired reduction in blood pressure. Increases in dose beyond 4 mg increase the likelihood of excessive postural effects including syncope, postural dizziness/vertigo and postural hypotension. At a titrated dose of 16 mg once daily the frequency of postural effects is about 12% compared to 3% for placebo.

HOW SUPPLIED

Doxazosin Tablets, USP are available as tablets for oral administration. Each tablet contains doxazosin mesylate equivalent to 1 mg, 2 mg, 4 mg or 8 mg of doxazosin.

The 1 mg are available as white to off-white, round, biconvex tablets debossed with M over D9 on one side of the tablet and scored on the other side. They are available as follows:

NDC 0378-4021-01
bottles of 100 tablets

The 2 mg are available as pink, round, biconvex tablets debossed with M over D10 on one side of the tablet and scored on the other side. They are available as follows:

NDC 0378-4022-01
bottles of 100 tablets

NDC 0378-4022-05
bottles of 500 tablets

The 4 mg are available as blue, round, biconvex tablets debossed with M over D11 on one side of the tablet and scored on the other side. They are available as follows:

NDC 0378-4024-01
bottles of 100 tablets

NDC 0378-4024-05
bottles of 500 tablets

The 8 mg are available as purple, round, biconvex tablets debossed with M over D12 on one side of the tablet and scored on the other side. They are available as follows:

NDC 0378-4028-01
bottles of 100 tablets

Store at 20° to 25°C (68° to 77°F). [See USP for Controlled Room Temperature.]

Dispense in a tight, light-resistant container as defined in the USP using a child-resistant closure.

PHARMACIST: Detach Patient Information Leaflet at each perforation and give leaflet to patient.

Mylan Pharmaceuticals Inc.
Morgantown, WV 26505

REVISED AUGUST 2007
DXZN:R6p

Information for Patients

(See Patient Leaflet)

Patients should be made aware of the possibility of syncopal and orthostatic symptoms, especially at the initiation of therapy, and urged to avoid driving or hazardous tasks for 24 hours after the first dose, after a dosage increase, and after interruption of therapy when treatment is resumed. They should be cautioned to avoid situations where injury could result should syncope occur during initiation of doxazosin therapy. They should also be advised of the need to sit or lie down when symptoms of lowered blood pressure occur, although these symptoms are not always orthostatic, and to be careful when rising from a sitting or lying position. If dizziness, lightheadedness, or palpitations are bothersome they should be reported to the physician, so that dose adjustment can be considered. Patients should also be told that drowsiness or somnolence can occur with doxazosin or any selective alpha1 adrenoceptor antagonist, requiring caution in people who must drive or operate heavy machinery.

Patients should be advised about the possibility of priapism as a result of treatment with alpha1 antagonists. Patients should know that this adverse event is very rare. If they experience priapism, it should be brought to immediate medical attention for if not treated promptly it can lead to permanent erectile dysfunction (impotence).

Drug/Laboratory Test Interactions

Doxazosin does not affect the plasma concentration of prostate specific antigen in patients treated for up to 3 years. Both doxazosin, an alpha1 inhibitor, and finasteride, a 5-alpha reductase inhibitor, are highly protein bound and hepatically metabolized. There is no definitive controlled clinical experience on the concomitant use of alpha1 inhibitors and 5-alpha reductase inhibitors at this time.

Impaired Liver Function

Doxazosin should be administered with caution to patients with evidence of impaired hepatic function or to patients receiving drugs known to influence hepatic metabolism (see CLINICAL PHARMACOLOGY).

Leukopenia/Neutropenia

Analysis of hematologic data from hypertensive patients receiving doxazosin in controlled hypertension clinical trials showed that the mean WBC (N = 474) and mean neutrophil counts (N = 419) were decreased by 2.4% and 1%, respectively, compared to placebo, a phenomenon seen with other alpha blocking drugs. In BPH patients the incidence of clinically significant WBC abnormalities was 0.4% (2/459) with doxazosin and 0% (0/147) with placebo, with no statistically significant difference between the two treatment groups. A search through a data base of 2,400 hypertensive patients and 665 BPH patients revealed 4 hypertensives in which drug-related neutropenia could not be ruled out and one BPH patient in which drug-related leukopenia could not be ruled out. Two hypertensives had a single low value on the last day of treatment. Two hypertensives had stable, non-progressive neutrophil counts in the 1000/mm^3 range over periods of 20 and 40 weeks. One BPH patient had a decrease from WBC count of 4800/mm^3 to 2700/mm^3 at the end of the study; there was no evidence of clinical impairment. In cases where follow-up was available the WBCs and neutrophil counts returned to normal after discontinuation of doxazosin. No patients became symptomatic as a result of the low WBC or neutrophil counts.

Drug Interactions

Most (98%) of plasma doxazosin is protein bound. In vitro data in human plasma indicate that doxazosin has no effect on protein binding of digoxin, warfarin, phenytoin or indomethacin. There is no information on the effect of other highly plasma protein bound drugs on doxazosin binding. Doxazosin has been administered without any evidence of an adverse drug interaction to patients receiving thiazide diuretics, beta-blocking agents, and nonsteroidal anti-inflammatory drugs. In a placebo-controlled trial in normal volunteers, the administration of a single 1 mg dose of doxazosin on day 1 of a 4-day regimen of oral cimetidine (400 mg twice daily) resulted in a 10% increase in mean AUC of doxazosin (p = 0.006), and a slight but not statistically significant increase in mean Cmax and mean half-life of doxazosin. The clinical significance of this increase in doxazosin AUC is unknown.

In clinical trials, doxazosin tablets have been administered to patients on a variety of concomitant medications; while no formal interaction studies have been conducted, no interactions were observed. Doxazosin tablets have been used with the following drugs or drug classes: 1) analgesic/anti-inflammatory (e.g., acetaminophen, aspirin, codeine and codeine combinations, ibuprofen, indomethacin); 2) antibiotics (e.g., erythromycin, trimethoprim and sulfamethoxazole, amoxicillin); 3) antihistamines (e.g., chlorpheniramine); 4) cardiovascular agents (e.g., atenolol, hydrochlorothiazide, propranolol); 5) corticosteroids; 6) gastrointestinal agents (e.g., antacids); 7) hypoglycemics and endocrine drugs; 8) sedatives and tranquilizers (e.g., diazepam); 9) cold and flu remedies.

Cardiac Toxicity in Animals

An increased incidence of myocardial necrosis or fibrosis was displayed by Sprague-Dawley rats after 6 months of dietary administration at concentrations calculated to provide 80 mg doxazosin/kg/day and after 12 months of dietary administration at concentrations calculated to provide 40 mg doxazosin/kg/day (AUC exposure in rats 8 times the human AUC exposure with a 12 mg/day therapeutic dose). Myocardial fibrosis was observed in both rats and mice treated in the same manner with 40 mg doxazosin/kg/day for 18 months (exposure 8 times human AUC exposure in rats and somewhat equivalent to human Cmax exposure in mice). No cardiotoxicity was observed at lower doses (up to 10 or 20 mg/kg/day, depending on the study) in either species. These lesions were not observed after 12 months of oral dosing in dogs at maximum doses of 20 mg/kg/day [maximum plasma concentrations (Cmax) in dogs 14 times the Cmax exposure in humans receiving a 12 mg/day therapeutic dose] and in Wistar rats at doses of 100 mg/kg/day (Cmax exposures 15 times human Cmax exposure with a 12 mg/day therapeutic dose). There is no evidence that similar lesions occur in humans.

Carcinogenesis, Mutagenesis, Impairment of Fertility

Chronic dietary administration (up to 24 months) of doxazosin mesylate at maximally tolerated doses of 40 mg/kg/day in rats and 120 mg/kg/day in mice revealed no evidence of carcinogenic potential. The highest doses evaluated in the rat and mouse studies are associated with AUCs (a measure of systemic exposure) that are 8 times and 4 times, respectively, the human AUC at a dose of 16 mg/day.

Mutagenicity studies revealed no drug- or metabolite-related effects at either chromosomal or subchromosomal levels.

Studies in rats showed reduced fertility in males treated with doxazosin at oral doses of 20 (but not 5 or 10) mg/kg/day, about 4 times the AUC exposures obtained with a 12 mg/day human dose. This effect was reversible within two weeks of drug withdrawal. There have been no reports of any effects of doxazosin on male fertility in humans.

Pregnancy Teratogenic Effects Pregnancy Category C

Studies in pregnant rabbits and rats at daily oral doses of up to 41 and 20 mg/kg, respectively (plasma drug concentrations 10 and 4 times human Cmax and AUC exposures with a 12 mg/day therapeutic dose), have revealed no evidence of harm to the fetus. A dosage regimen of 82 mg/kg/day in the rabbit was associated with reduced fetal survival. There are no adequate and well-controlled studies in pregnant women. Because animal reproduction studies are not always predictive of human response, doxazosin should be used during pregnancy only if clearly needed.

Radioactivity was found to cross the placenta following oral administration of labeled doxazosin to pregnant rats.

Nonteratogenic Effects

In peri-postnatal studies in rats, postnatal development at maternal doses of 40 or 50 mg/kg/day of doxazosin (8 times human AUC exposure with a 12 mg/day therapeutic dose) was delayed as evidenced by slower body weight gain and a slightly later appearance of anatomical features and reflexes.

Nursing Mothers

Studies in lactating rats given a single oral dose of 1 mg/kg of [2-^14C]-doxazosin indicate that doxazosin accumulates in rat breast milk with a maximum concentration about 20 times greater than the maternal plasma concentration. It is not known whether this drug is excreted in human milk. Because many drugs are excreted in human milk, caution should be exercised when doxazosin is administered to a nursing mother.

Pediatric Use

The safety and effectiveness of doxazosin as an antihypertensive agent have not been established in pediatric patients.

Geriatric Use

The safety and effectiveness profile of doxazosin in BPH was similar in the elderly (age ≥ 65 years) and younger (age less 65 years) patients.

Clinical studies of doxazosin did not include sufficient numbers of subjects aged 65 and over to determine whether they respond differently from younger subjects. Other reported clinical experience has not identified differences in responses between the elderly and younger patients. In general, dose selection for an elderly patient should be cautious, usually starting at the low end of the dosing range, reflecting the greater frequency of decreased hepatic, renal, or cardiac function, and of concomitant disease or other drug therapy.

PACKAGE LABEL

doxazosin4mg